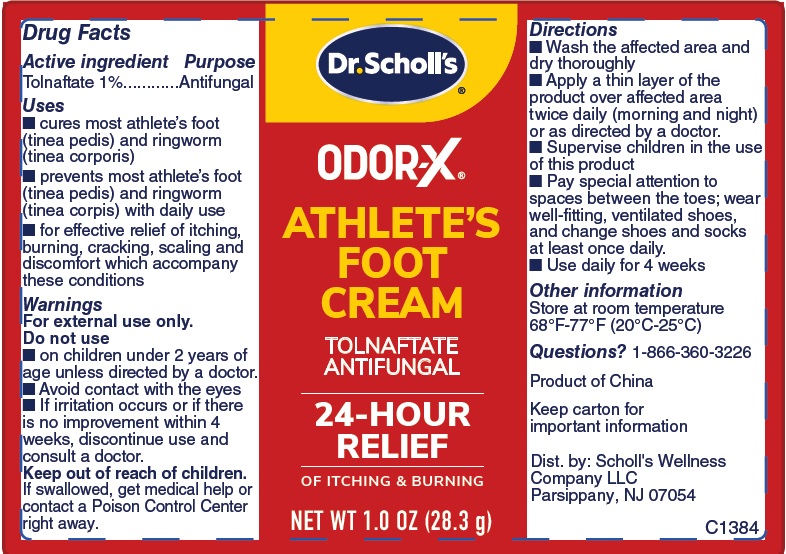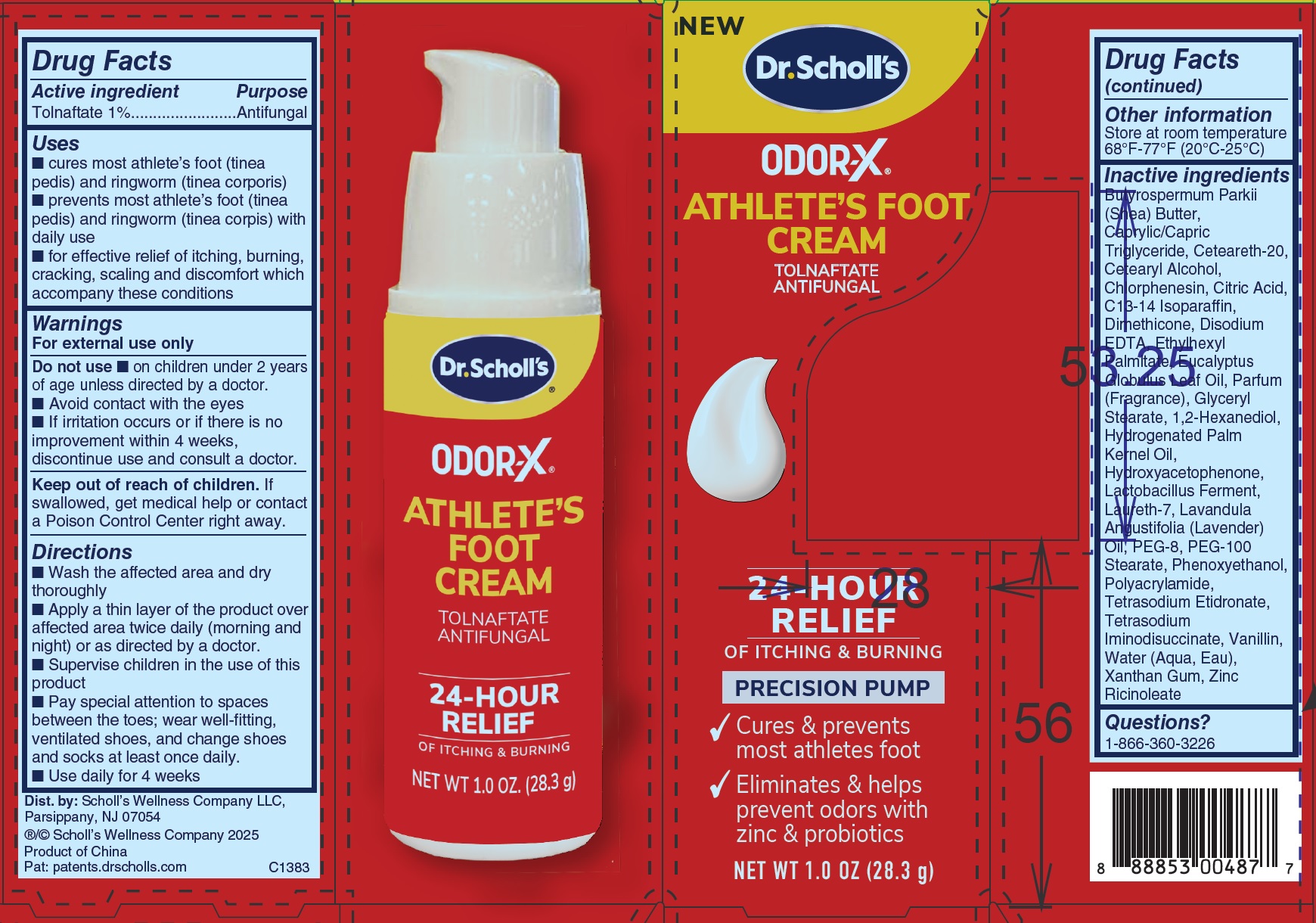 DRUG LABEL: Dr.Scholl s Odor X Athlete s Foot
NDC: 73469-0618 | Form: CREAM
Manufacturer: Scholl's Wellness Company LLC
Category: otc | Type: HUMAN OTC DRUG LABEL
Date: 20260129

ACTIVE INGREDIENTS: TOLNAFTATE 10 mg/1 g
INACTIVE INGREDIENTS: POLYACRYLAMIDE (CROSSLINKED; 0.01-0.2 MOLE PERCENT BISACRYLAMIDE); LIMOSILACTOBACILLUS FERMENTUM; CETEARETH-20; SHEA BUTTER; MEDIUM-CHAIN TRIGLYCERIDES; CETEARYL ALCOHOL; CHLORPHENESIN; CITRIC ACID MONOHYDRATE; C13-14 ISOPARAFFIN; DIMETHICONE; EDETATE DISODIUM; ETHYLHEXYL PALMITATE; EUCALYPTUS GLOBULUS LEAF OIL; GLYCERYL MONOSTEARATE; 1,2-HEXANEDIOL; HYDROGENATED PALM KERNEL OIL; HYDROXYACETOPHENONE; LAURETH-7; LAVENDER OIL; POLYETHYLENE GLYCOL 400; PEG-100 MONOSTEARATE; PHENOXYETHANOL; ETIDRONATE TETRASODIUM; TETRASODIUM IMINODISUCCINATE; VANILLIN; WATER; XANTHAN GUM; ZINC RICINOLEATE

Dr.Scholl's Odor-X Athlete's Foot Cream

Active ingredient

Tolnaftate 1%

Purpose

Antifungal

Uses

- cures most athlete’s foot (tinea pedis) and ringworm (tinea corporis)
- prevents most athlete’s foot (tinea pedis) and ringworm (tinea corpis) with daily use
- for effective relief of itching, burning, cracking, scaling and discomfort which accompany these conditions

Warnings

For external use only

Do not use

- on children under 2 years of age unless directed by a doctor.
- Avoid contact with the eyes
- If irritation occurs or if there is no improvement within 4 weeks, discontinue use and consult a doctor.

Keep out of reach of children.

If swallowed, get medical help or contact a Poison Control Center right away.

Directions

- Wash the affected area and dry thoroughly
- Apply a thin layer of the product over affected area twice daily (morning and night) or as directed by a doctor.
- Supervise children in the use of this product
- Pay special attention to spaces between the toes; wear well-fitting, ventilated shoes, and change shoes and socks at least once daily.
- Use daily for 4 weeks

Other information

Store at room temperature 68°F-77°F (20°C-25°C)

Inactive ingredients

Butyrospermum Parkii (Shea) Butter, Caprylic/Capric Triglyceride, Ceteareth-20, Cetearyl Alcohol, Chlorphenesin, Citric Acid, C13-14 Isoparaffin, Dimethicone, Disodium EDTA, Ethylhexyl Palmitate, Eucalyptus Globulus Leaf Oil, Parfum (Fragrance), Glyceryl Stearate, 1,2-Hexanediol, Hydrogenated Palm Kernel Oil, Hydroxyacetophenone, Lactobacillus Ferment, Laureth-7, Lavandula Angustifolia (Lavender) Oil, PEG-8, PEG-100 Stearate, Phenoxyethanol, Polyacrylamide, Tetrasodium Etidronate, Tetrasodium Iminodisuccinate, Vanillin, Water (Aqua, Eau), Xanthan Gum, Zinc Ricinoleate

Questions?

1-866-360-3226